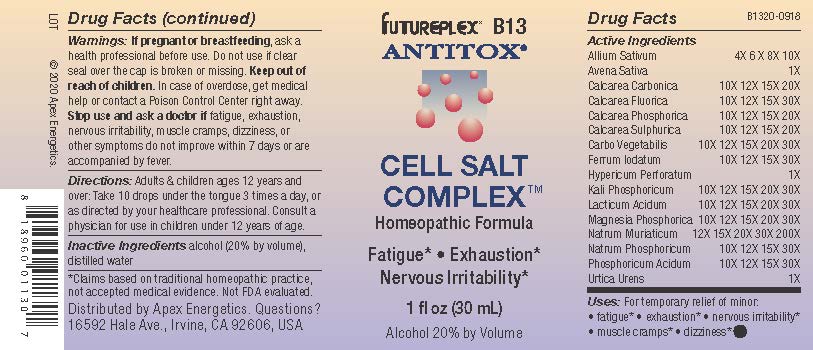 DRUG LABEL: B13
NDC: 63479-0213 | Form: SOLUTION/ DROPS
Manufacturer: Apex Energetics Inc.
Category: homeopathic | Type: HUMAN OTC DRUG LABEL
Date: 20240108

ACTIVE INGREDIENTS: POTASSIUM PHOSPHATE, DIBASIC 30 [hp_X]/1 mL; GARLIC 10 [hp_X]/1 mL; OYSTER SHELL CALCIUM CARBONATE, CRUDE 20 [hp_X]/1 mL; MAGNESIUM PHOSPHATE, DIBASIC TRIHYDRATE 30 [hp_X]/1 mL; CALCIUM FLUORIDE 30 [hp_X]/1 mL; TRIBASIC CALCIUM PHOSPHATE 20 [hp_X]/1 mL; SODIUM CHLORIDE 200 [hp_X]/1 mL; SODIUM PHOSPHATE, DIBASIC, HEPTAHYDRATE 30 [hp_X]/1 mL; CALCIUM SULFATE ANHYDROUS 20 [hp_X]/1 mL; ACTIVATED CHARCOAL 30 [hp_X]/1 mL; HYPERICUM PERFORATUM 1 [hp_X]/1 mL; LACTIC ACID, DL- 30 [hp_X]/1 mL; FERROUS IODIDE 30 [hp_X]/1 mL; AVENA SATIVA FLOWERING TOP 1 [hp_X]/1 mL; PHOSPHORIC ACID 30 [hp_X]/1 mL; URTICA URENS 1 [hp_X]/1 mL
INACTIVE INGREDIENTS: WATER; ALCOHOL

B13

Active Ingredients
Allium Sativum | 4X 6 X 8X 10X
Avena Sativa | 1X
Calcarea Carbonica | 10X 12X 15X 20X
Calcarea Fluorica | 10X 12X 15X 30X
Calcarea Phosphorica | 10X 12X 15X 20X
Calcarea Sulphurica | 10X 12X 15X 20X
Carbo Vegetabilis | 10X 12X 15X 20X 30X
Ferrum Iodatum | 10X 12X 15X 30X
Hypericum Perforatum | 1X
Kali Phosphoricum | 10X 12X 15X 20X 30X
Lacticum Acidum | 10X 12X 15X 20X 30X
Magnesia Phosphorica | 10X 12X 15X 20X 30X
Natrum Muriaticum | 12X 15X 20X 30X 200X
Natrum Phosphoricum | 10X 12X 15X 30X
Phosphoricum Acidum | 10X 12X 15X 30X
Urtica Urens | 1X

INDICATIONS AND USAGE

Uses:

For temporary relief of minor:

fatigue*

exhaustion*

nervous irritability*

muscle cramps*

dizziness*

* Claims based on traditional homeopathic practice, not accepted medical evidence. Not FDA evaluated.

Warnings:

PREGNANCY OR BREAST FEEDING

If pregnant or breastfeeding, ask a health professional before use.

Do not use if clear seal over the cap is broken or missing.

Keep out of reach of children. In case of overdose, get medical help or contact a Poison Control Center right away.

Stop use and ask a doctor if fatigue, exhaustion, nervous irritability, muscle cramps, dizziness, or other symptoms do not improve within 7 days or are accompanied by fever.

Directions:

Adults & children ages 12 years and over: Take 10 drops under the tongue 3 times a day, or as directed by your healthcare professional. Consult a physician for use in children under 12 years of age.

Inactive Ingredients

alcohol (20% by volume), distilled water

Distributed by Apex Energetics. Questions?

16592 Hale Ave., Irvine, CA 92606, USA

PACKAGE LABEL

FUTUREPLEX® B13

ANTITOX®

CELL SALT COMPLEX™

Homeopathic Formula

Fatigue* Exhaustion*

Nervous Irritability*

1 fl oz (30 mL)

Alcohol 20% by Volume